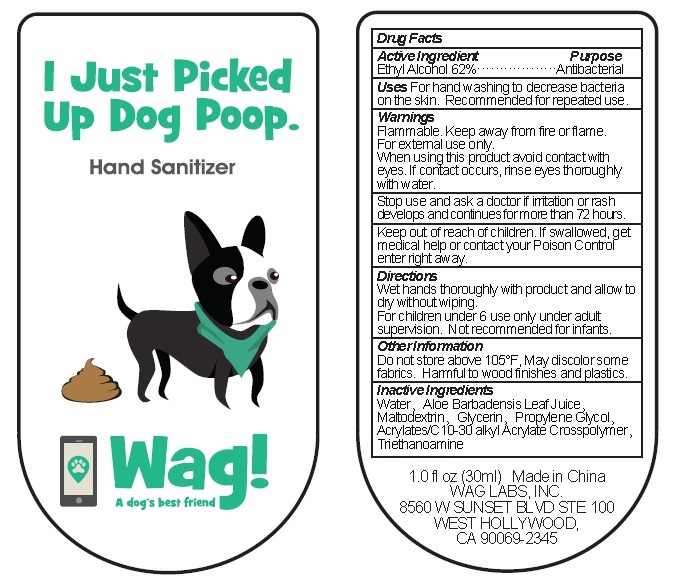 DRUG LABEL: Hand Sanitizer
NDC: 71828-001 | Form: GEL
Manufacturer: WAG LABS, INC.
Category: otc | Type: HUMAN OTC DRUG LABEL
Date: 20171101

ACTIVE INGREDIENTS: ALCOHOL 62 mL/100 mL
INACTIVE INGREDIENTS: MALTODEXTRIN; WATER; ALOE VERA LEAF; GLYCERIN; PROPYLENE GLYCOL; CARBOMER INTERPOLYMER TYPE A (55000 CPS); TROLAMINE

Active Ingredient:
Ethyl Alcohol 62%

Purpose

Antibacterial

Warnings

Flammable. Keep away from fire or flame.

For external use only.

Stop use and ask a doctor if irritation or rash develops and continues for more that 72 hours.

Keep out of reach of children. If swallowed, get medical help or contact your Poison Control Center right away.

Directions

Wet hands thoroughly with product and allow to dry without wiping.

For children under 6 use only under adult supervision. Not recommended for infants.

Inactive Ingredients

Water, Aloe Barbadensis Leaf Juice, Maltodextrin, Glycerin, Propylene Glycol, Acrylates/C10-30 Alkyl Acrylate Crosspolymer, Triethanoamine

Other Information

Do not store above 105F. May discolor some fabrics. Harmful to wood finishes and plastics

Uses

For hand washing to decrease bacteria on the skin. Recommended for repeated use.

When using this product avoid contact with eyes. If contact occurs, rinse eyes thoroughly with water.